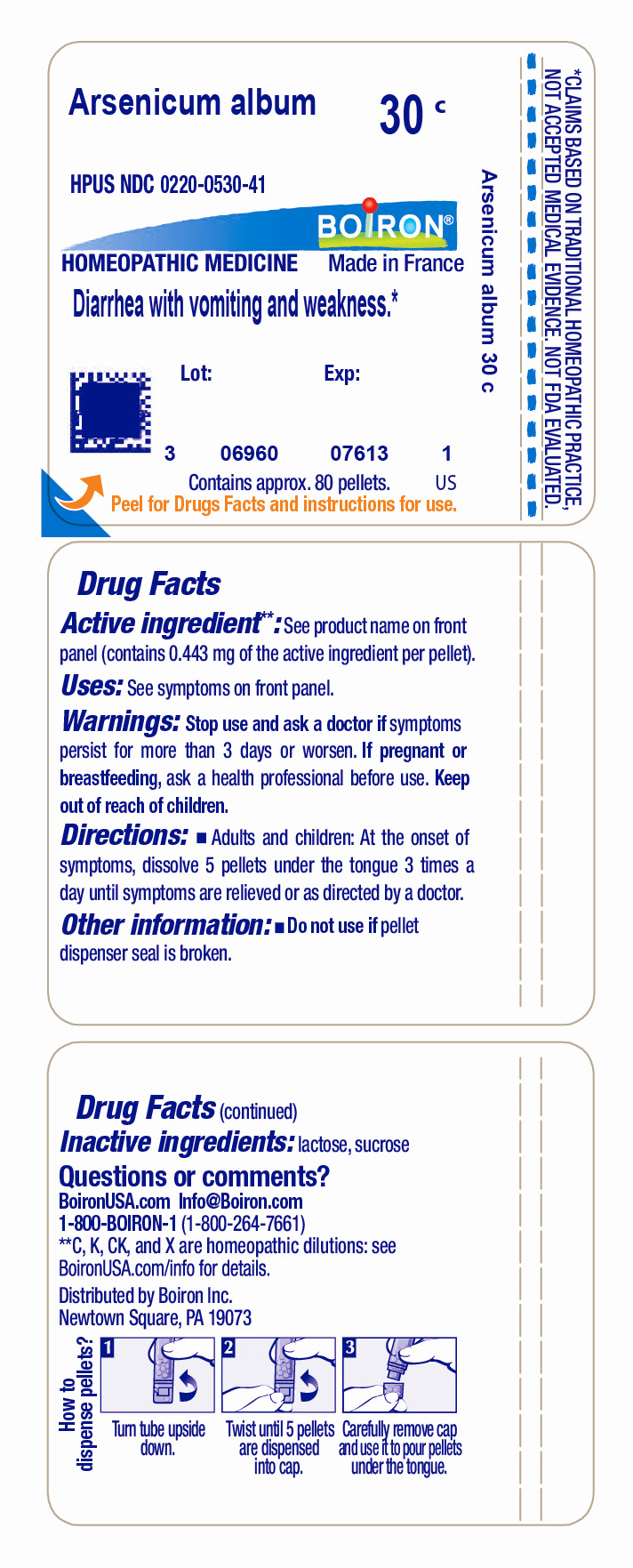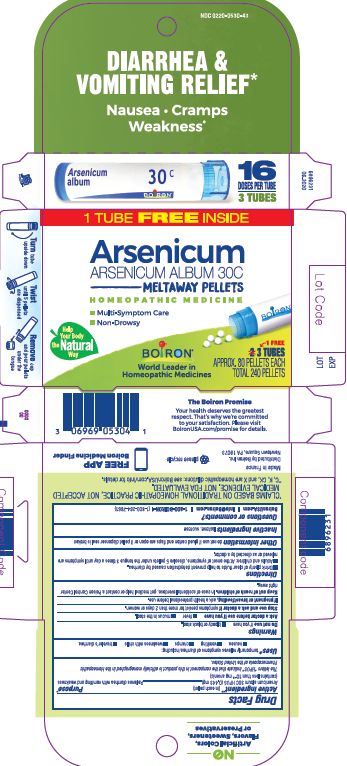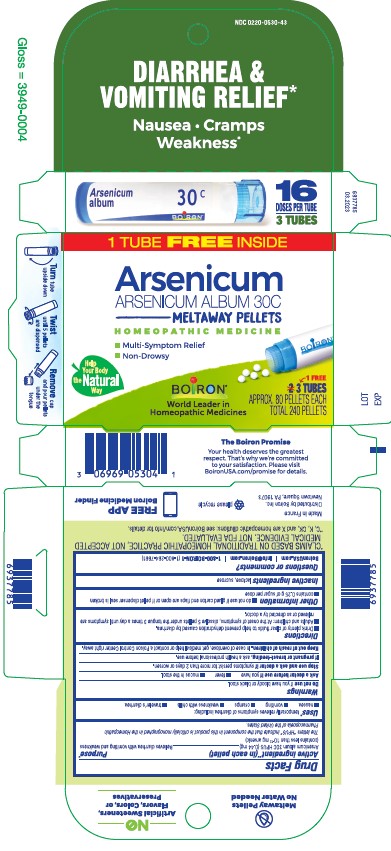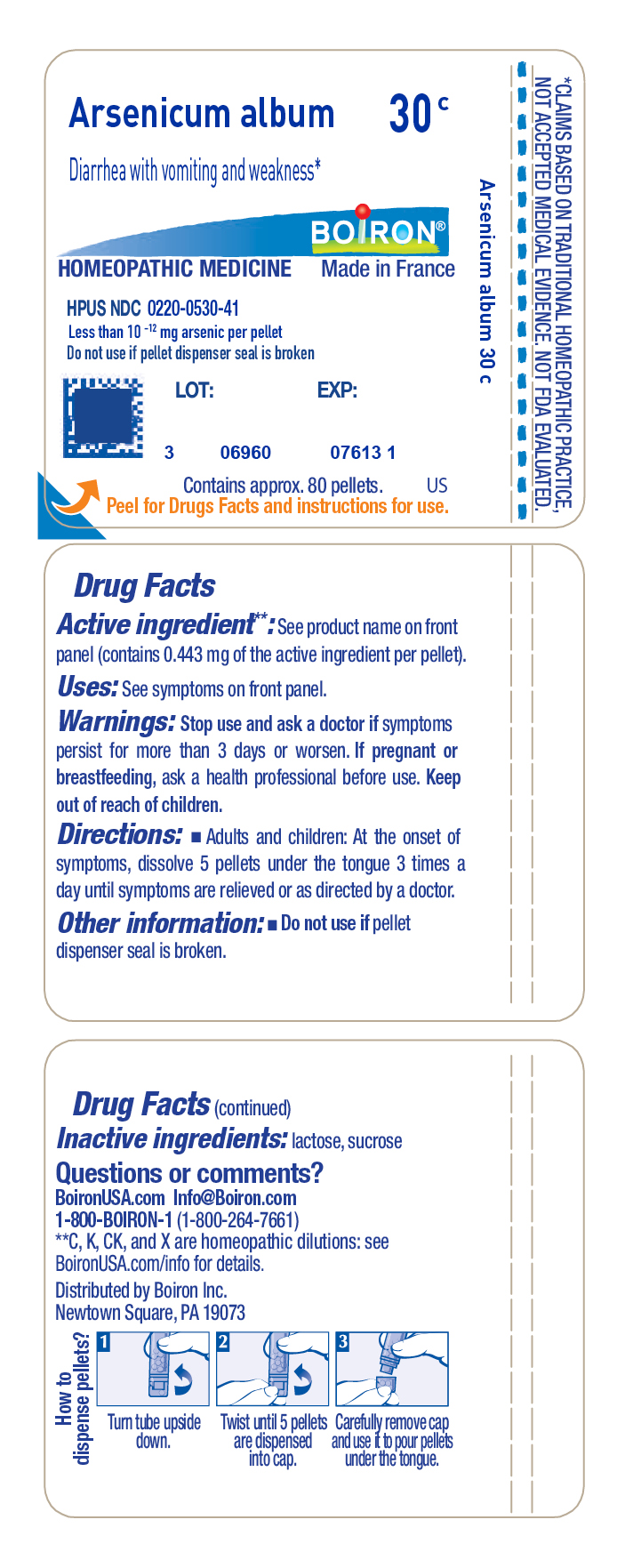 DRUG LABEL: Arsenicum album
NDC: 0220-0530 | Form: PELLET
Manufacturer: Boiron
Category: homeopathic | Type: HUMAN OTC DRUG LABEL
Date: 20230726

ACTIVE INGREDIENTS: ARSENIC TRIOXIDE 30 [hp_C]/30 [hp_C]
INACTIVE INGREDIENTS: LACTOSE, UNSPECIFIED FORM; SUCROSE

Arsenicum album 30C

Active ingredient** (in each pellet)

Box - Arsenicum album 30C HPUS (0.44 mg)(contains less than 10^-12 mg arsenic)

Tube - Arsenicum album 30C HPUS (**contains 0.443 mg of the active ingredient per pellet) (contains less than 10^-12 mg arsenic)

The letters "HPUS" indicate that the components in this product are officially monographed in the Homeopathic Pharmacopoeia of the United States.

Purpose*

Box - Relieves diarrhea with vomiting and weakness

Uses*

Box - temporarily relieves symptoms of diarrhea including: nausea, vomiting, cramps, weakness with chills, traveler's diarrhea

Tube - Diarrhea With Vomiting And Weakness*

DO NOT USE

Box - Do not use if you have: bloody or black stool.

ASK DOCTOR

Box - As a doctor before using if you have: fever, mucus in stool

STOP USE

Box - Stop use and ask a doctor if symptoms persist for more than 2 days or worsen.

Tube - Stop use and ask a doctor if symptoms persist for more than 3 days or worsen.

PREGNANCY OR BREAST FEEDING

Box - If pregnant or breast-feeding, ask a health professional before use.

Tube - If pregnant or breast-feeding, ask a health professional before use.

KEEP OUT OF REACH OF CHILDREN

Box - Keep out of reach of children. In case of overdose, get medical help or contact a Poison Control Center right away.

Tube - Keep out of reach of children.

DOSAGE AND ADMINISTRATION

Box - Drink plenty of clear fluids to help prevent dehydration caused by diarrhea. Adults and children: At the onset of symptoms, dissolve 5 pellets under the tongue 3 times a day until symptoms are relieved or as directed by a doctor.

Tube - Adults and children: At the onset of symptoms, dissolve 5 pellets under the tongue 3 times a day until symptoms are relieved or as directed by a doctor.

INACTIVE INGREDIENT

Box - lactose, sucrose

Tube - lactose, sucrose

QUESTIONS

Tube - 1-800-BOIRON-1 (1-800-264-7661),
BoironUSA.com Info@boiron.com
Distributed by Boiron, Inc. Newtown Square, PA 19073

Box - 1-800-BOIRON-1 (1-800-264-7661),
BoironUSA.com Info@boiron.com
Distributed by Boiron, Inc. Newtown Square, PA 19073

Box - do not use if glued carton end flaps are open or if pellet dispenser seal is broken.

contains 0.25 g of sugar per dose

3 Tubes

Approx. 80 pellets each

Total 240 pellets

16 Doses per tube

Turn tube upside down. Twist until 5 pellets are dispensed. Remove cap and pour pellets under the tongue.

Diarrhea & Vomiting Relief*

Nausea Cramps Weakness*

Multi-Symptom Relief

Non-drowsy

Meltaway Pellets
*CLAIMS BASED ON TRADITIONAL HOMEOPATHIC PRACTICE NOT ACCEPTED MEDICAL EVIDENCE. NOT FDA EVALUATED.
*C,K,CK, and X are homeopathic dilutions: see BoironUSA.com/info for details.

Tube- Do not use if pellet dispenser seal is broken.
Contains approx 80 pellets.
How to dispense pellets? Turn tube upside down. Twist until 5 pellets are dispensed into cap. Carefully remove the cap and use it to pour pellets under the tongue.
*CLAIMS BASED ON TRADITIONAL HOMEOPATHIC PRACTICE NOT ACCEPTED MEDICAL EVIDENCE. NOT FDA EVALUATED.
*C,K,CK, and X are homeopathic dilutions: see BoironUSA.com/info for details.